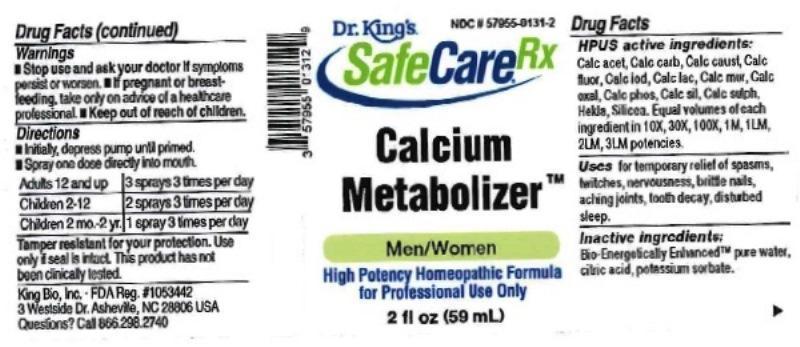 DRUG LABEL: Calcium Metabolizer
NDC: 57955-0131 | Form: LIQUID
Manufacturer: King Bio Inc.
Category: homeopathic | Type: HUMAN OTC DRUG LABEL
Date: 20161202

ACTIVE INGREDIENTS: CALCIUM ACETATE 10 [hp_X]/59 mL; OYSTER SHELL CALCIUM CARBONATE, CRUDE 10 [hp_X]/59 mL; CALCIUM HYDROXIDE 10 [hp_X]/59 mL; CALCIUM FLUORIDE 10 [hp_X]/59 mL; CALCIUM IODIDE 10 [hp_X]/59 mL; CALCIUM LACTATE PENTAHYDRATE 10 [hp_X]/59 mL; CALCIUM CHLORIDE 10 [hp_X]/59 mL; CALCIUM OXALATE MONOHYDRATE 10 [hp_X]/59 mL; TRIBASIC CALCIUM PHOSPHATE 10 [hp_X]/59 mL; CALCIUM SILICATE 10 [hp_X]/59 mL; CALCIUM SULFATE ANHYDROUS 10 [hp_X]/59 mL; HEKLA LAVA 10 [hp_X]/59 mL; SILICON DIOXIDE 10 [hp_X]/59 mL
INACTIVE INGREDIENTS: WATER; ANHYDROUS CITRIC ACID; POTASSIUM SORBATE

Calcium Metabolizer™

ACTIVE INGREDIENT

Drug Facts__________________________________________________________________________________________________________

HPUS active ingredients: Calcarea acetica, Calcarea carbonica, Calcarea caustica, Calcarea fluorica, Calcarea iodata, Calcarea lactica, Calcarea muriatica, Calcarea oxalica, Calcarea phosphorica, Calcarea silicata, Calcarea sulphurica, Hekla lava, Silicea. Equal volumes of each ingredient in 10X, 30X, 100X, 1M, 1LM, 2LM, 3LM potencies.

INDICATIONS AND USAGE

Uses for temporary relief of spasms, twitches, nervousness, brittle nails, aching joints, tooth decay, disturbed sleep.

INACTIVE INGREDIENT

Inactive Ingredients: Bio-Energetically Enhanced™ pure water, citric acid and potassium sorbate.

Warnings

- Stop use and ask your doctor if symptoms persist or worsen.
- If pregnant or breast-feeding, take only on advice of a healthcare professional.

- Keep out of reach of children.

Directions

- Initially, depress pump until primed.
- Spray one dose directly into mouth.
- Adults 12 and up: 3 sprays 3 times per day.
- Children 2-12: 2 sprays 3 times per day.
- Children 2 mo-2 yr: 1 spray 3 times per day.

OTHER SAFETY INFORMATION

Tamper resistant for your protection. Use only if seal is intact. This product has not been independently tested.

PURPOSE

Uses for temporary relief of:

- spasms
- twitches
- nervousness
- brittle nails,
- aching joints
- tooth decay
- disturbed sleep